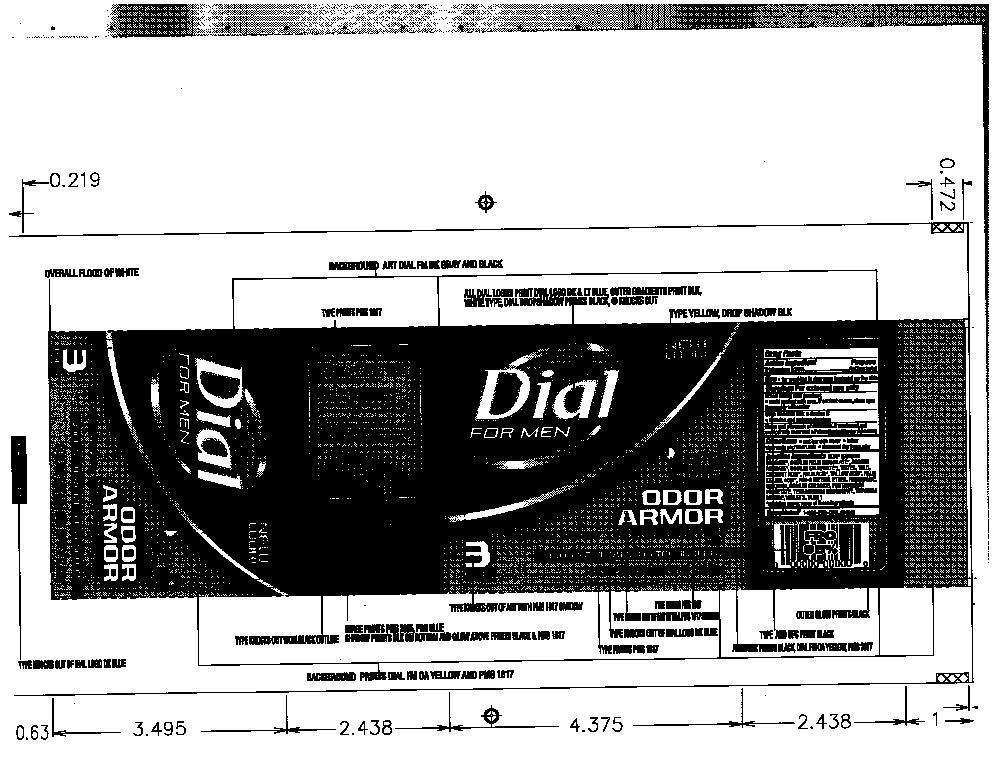 DRUG LABEL: Dial Odor Armor
NDC: 51815-303 | Form: SOAP
Manufacturer: VVF Illinois Services LLC
Category: otc | Type: HUMAN OTC DRUG LABEL
Date: 20140527

ACTIVE INGREDIENTS: TRICLOCARBAN 1.017 g/339 g
INACTIVE INGREDIENTS: SODIUM COCOATE; SODIUM PALM KERNELATE; SODIUM PALMATE; SODIUM TALLOWATE, BEEF; Water; TALC; COCONUT ACID; PALM ACID; TALLOW ACID, BEEF; PALM KERNEL ACID; PEG-6 METHYL ETHER; GLYCERIN; SODIUM CHLORIDE; PENTASODIUM PENTETATE; ETIDRONATE TETRASODIUM; TITANIUM DIOXIDE; D&C VIOLET NO. 2; FD&C BLUE NO. 1

Dial Odor Armor

ACTIVE INGREDIENT

TRICLOCARBAN

PURPOSE

ANTIBACTERIAL

KEEP OUT OF REACH OF CHILDREN

If swallowed, get medical

help or contact Poison Control right away.

USE

For washing to decrease bacteria on the skin

WARNINGS

For external use only

When using this product

Avoid contact with eyes. In case of eye contact, flush with water

Stop using and ask doctor if irritation and redness develops

USE

wet bar with water - lather vigorously -

and wash skin - rinse and dry thoroughly

QUESTIONS

1-800-258 (DIAL)

Inactive Ingredients

SOAP (SODIUM COCOATE, SODIUM PALM KERNELATE, SODIUM PALMATE, SODIUM TALLOWATE), WATER, TALC, COCONUT ACID, PALM ACID, TALLOW ACID, PALM KERNEL ACID, PEG-6 METHYL ETHER, FRAGRANCE, GLYCERIN, SODIUM CHLORIDE, PENTASODIUM PENTETATE, TETRASODIUM ETIDRONATE, TITANIUM DIOXIDE, VIOLET 2 , BLUE 1